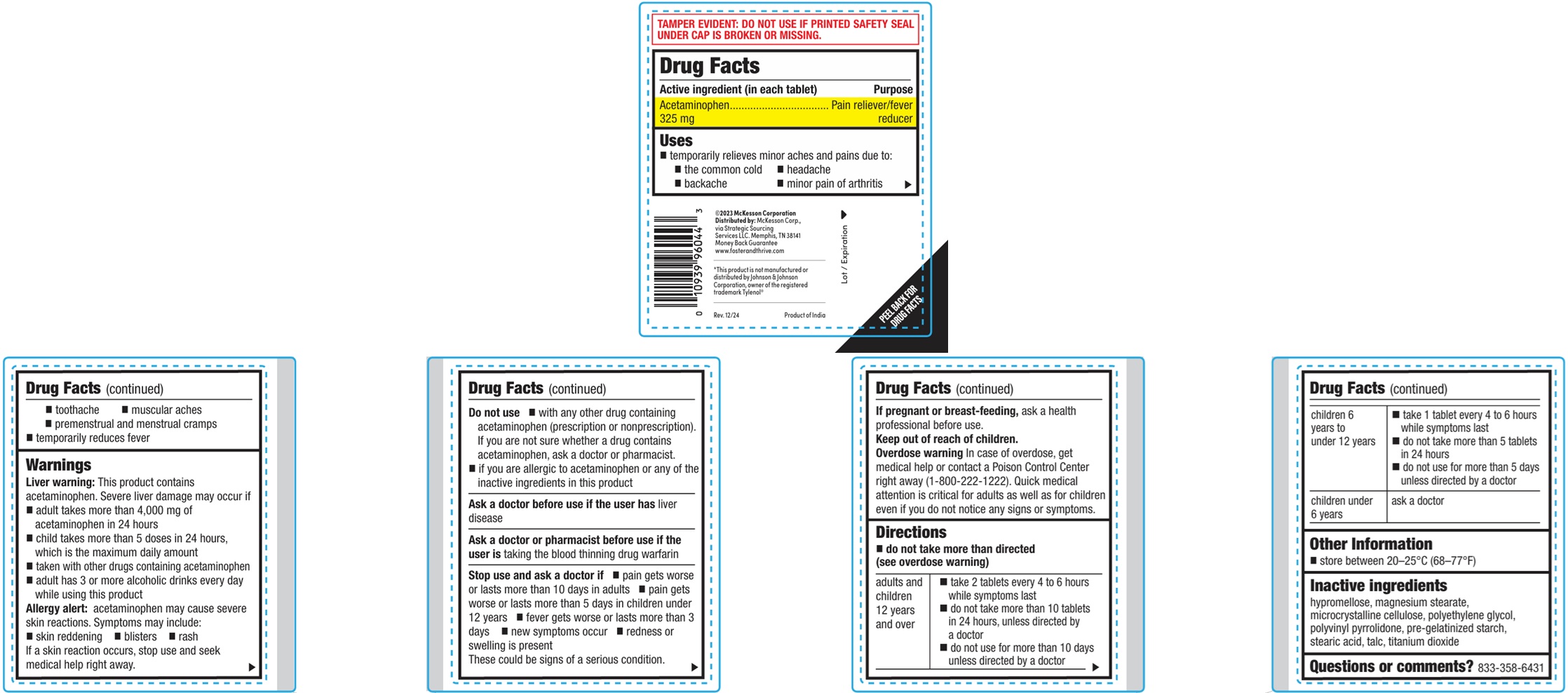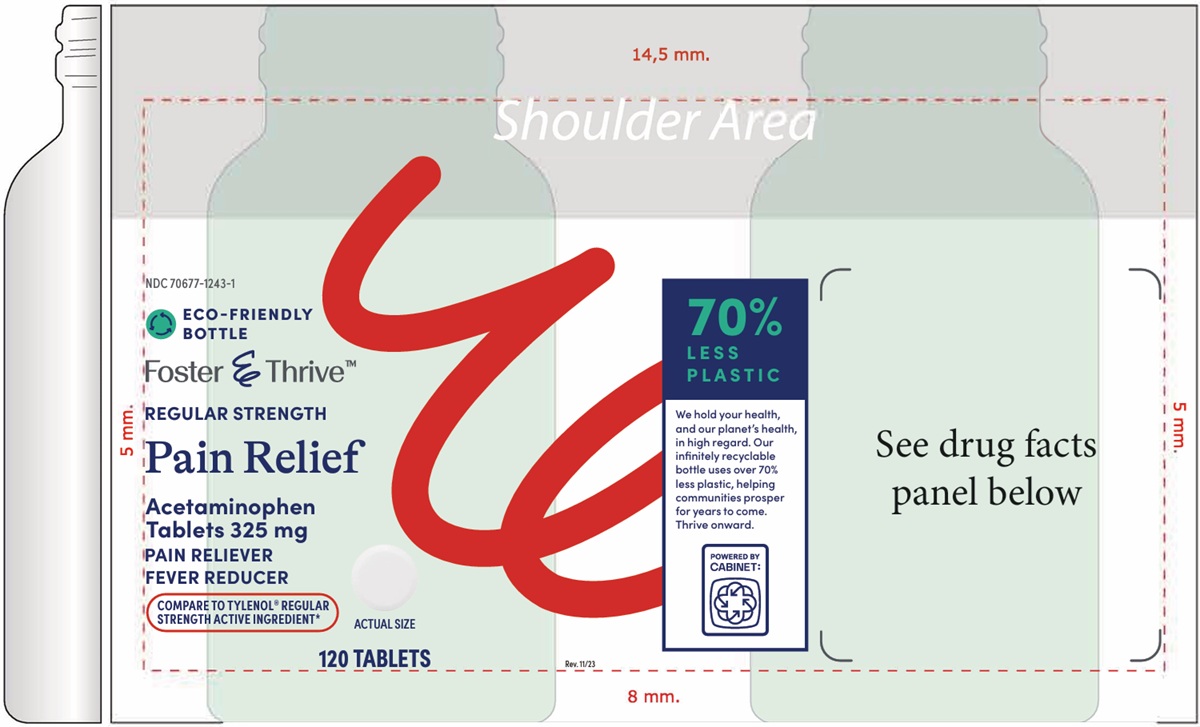 DRUG LABEL: Regular Strength Pain Reliever
NDC: 70677-1243 | Form: TABLET, FILM COATED
Manufacturer: Strategic Sourcing Services, LLC
Category: otc | Type: HUMAN OTC DRUG LABEL
Date: 20260129

ACTIVE INGREDIENTS: ACETAMINOPHEN 325 mg/1 1
INACTIVE INGREDIENTS: HYPROMELLOSES; MAGNESIUM STEARATE; MICROCRYSTALLINE CELLULOSE; POLYETHYLENE GLYCOL, UNSPECIFIED; POVIDONE; STARCH, CORN; STEARIC ACID; TALC; TITANIUM DIOXIDE

Regular Strength Pain Reliever